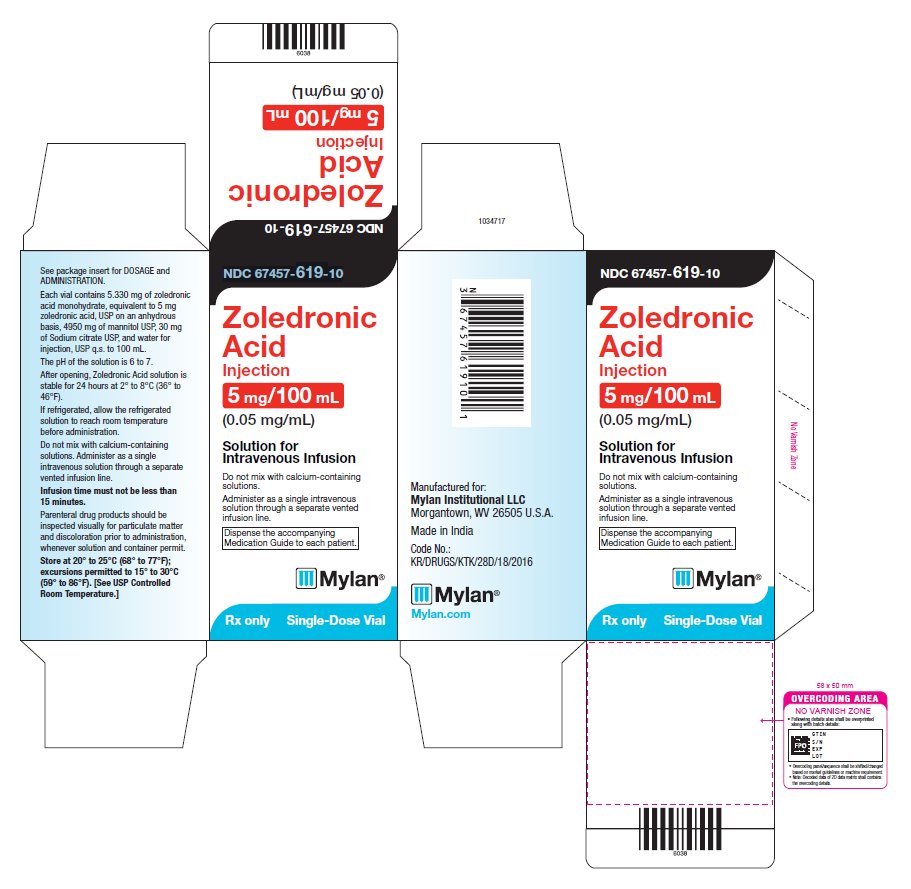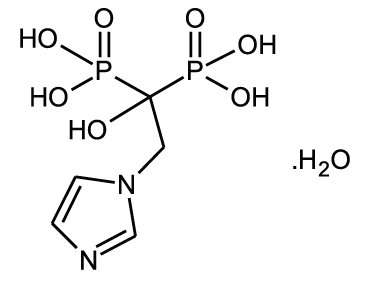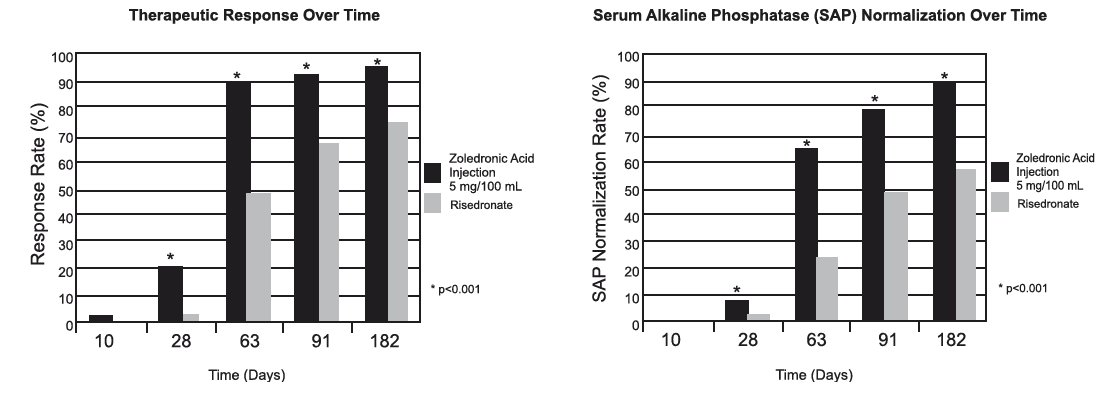 DRUG LABEL: Zoledronic Acid
NDC: 67457-619 | Form: INJECTION, SOLUTION
Manufacturer: Mylan Institutional LLC
Category: prescription | Type: HUMAN PRESCRIPTION DRUG LABEL
Date: 20231015

ACTIVE INGREDIENTS: ZOLEDRONIC ACID 5 mg/100 mL
INACTIVE INGREDIENTS: SODIUM CITRATE, UNSPECIFIED FORM; MANNITOL; WATER

HIGHLIGHTS OF PRESCRIBING INFORMATION

These highlights do not include all the information needed to use ZOLEDRONIC ACID INJECTION safely and effectively. See full prescribing information for ZOLEDRONIC ACID INJECTION.
ZOLEDRONIC ACID injection, for intravenous infusion
Initial U.S. Approval: 2001

1 INDICATIONS AND USAGE

Zoledronic acid injection is a bisphosphonate indicated for:

- Treatment of Paget’s disease of bone in men and women (1.5)

2 DOSAGE AND ADMINISTRATION

Infusion given intravenously over no less than 15 minutes:

- Treatment of Paget’s disease of bone: a single 5 mg infusion. Patients should receive 1500 mg elemental calcium and 800 international units vitamin D daily (2.6)

3 DOSAGE FORMS AND STRENGTHS

5 mg in a 100 mL ready-to-infuse solution (3)

4 CONTRAINDICATIONS

- Hypocalcemia (4)
- Patients with creatinine clearance less than 35 mL/min and in those with evidence of acute renal impairment (4, 5.3)
- Hypersensitivity to any component of zoledronic acid injection (4, 6.2)

5 WARNINGS AND PRECAUTIONS

- Products Containing Same Active Ingredient: Patients receiving Zometa should not receive zoledronic acid (5.1)
- Hypocalcemia may worsen during treatment. Patients must be adequately supplemented with calcium and vitamin D (5.2)
- Renal Impairment: A single dose should not exceed 5 mg and the duration of infusion should be no less than 15 minutes. Renal toxicity may be greater in patients with underlying renal impairment or with other risk factors, including advanced age or dehydration. Monitor creatinine clearance before each dose (2.7, 5.3)
- Osteonecrosis of the Jaw (ONJ) has been reported. All patients should have a routine oral exam by the prescriber prior to treatment (5.4)
- Atypical Femur Fractures have been reported. Patients with thigh or groin pain should be evaluated to rule out a femoral fracture (5.5)
- Severe Bone, Joint, and Muscle Pain may occur. Withhold future doses of zoledronic acid if severe symptoms occur (5.7)

6 ADVERSE REACTIONS

The most common adverse reactions (greater than 10%) were pyrexia, myalgia, headache, arthralgia, pain in extremity (6.1). Other important adverse reactions were flu-like illness, nausea, vomiting, diarrhea (6.2), and eye inflammation (6.1).

To report SUSPECTED ADVERSE REACTIONS, contact Mylan at 1-877-446-3679 (1-877-4-INFO-RX) or FDA at 1-800-FDA-1088 or www.fda.gov/medwatch.

7 DRUG INTERACTIONS

- Aminoglycosides: May lower serum calcium for prolonged periods (7.1)
- Loop diuretics: May increase risk of hypocalcemia (7.2)
- Nephrotoxic drugs: Use with caution (7.3)
- Drugs primarily excreted by the kidney: Exposure may be increased with renal impairment. Monitor serum creatinine in patients at risk (7.4)

8 USE IN SPECIFIC POPULATIONS

- Pregnancy: Discontinue when pregnancy is recognized (8.1)
- Pediatric Use: Not indicated for use in pediatric patients (8.4)
- Geriatric Use: Special care to monitor renal function (8.5)

FULL PRESCRIBING INFORMATION

1 INDICATIONS AND USAGE

1.5 Paget’s Disease of Bone

Zoledronic acid injection is indicated for treatment of Paget’s disease of bone in men and women. Treatment is indicated in patients with Paget’s disease of bone with elevations in serum alkaline phosphatase of two times or higher than the upper limit of the age-specific normal reference range, or those who are symptomatic, or those at risk for complications from their disease [see Clinical Studies (14.5)].

2 DOSAGE AND ADMINISTRATION

2.1 Important Administration Instructions

Zoledronic acid injection must be administered as an intravenous infusion over no less than 15 minutes.

- Patients must be appropriately hydrated prior to administration of zoledronic acid injection [see Warnings and Precautions (5.3)].
- Parenteral drug products should be inspected visually for particulate matter and discoloration prior to administration, whenever solution and container permit.
- Intravenous infusion should be followed by a 10 mL normal saline flush of the intravenous line.
- Administration of acetaminophen following zoledronic acid injection administration may reduce the incidence of acute-phase reaction symptoms.

2.6 Treatment of Paget’s Disease of Bone

The recommended dose is a 5 mg infusion. The infusion time must not be less than 15 minutes given over a constant infusion rate.

Re-treatment of Paget’s Disease

After a single treatment with zoledronic acid injection in Paget’s disease an extended remission period is observed. Specific re-treatment data are not available. However, re-treatment with zoledronic acid injection may be considered in patients who have relapsed, based on increases in serum alkaline phosphatase, or in those patients who failed to achieve normalization of their serum alkaline phosphatase, or in those patients with symptoms, as dictated by medical practice.

2.7 Laboratory Testing and Oral Examination Prior to Administration

- Prior to administration of each dose of zoledronic acid injection, obtain a serum creatinine and creatinine clearance should be calculated based on actual body weight using Cockcroft-Gault formula before each zoledronic acid injection dose. Zoledronic acid injection is contraindicated in patients with creatinine clearance less than 35 mL/min and in those with evidence of acute renal impairment. A 5 mg dose of zoledronic acid injection administered intravenously is recommended for patients with creatinine clearance greater than or equal to 35 mL/min. There are no safety or efficacy data to support the adjustment of the zoledronic acid injection dose based on baseline renal function. Therefore, no dose adjustment is required in patients with CrCl greater than or equal to 35 mL/min [see Contraindications (4), Warnings and Precautions (5.3)].
- A routine oral examination should be performed by the prescriber prior to initiation of zoledronic acid injection treatment [see Warnings and Precautions (5.4)].

2.8 Calcium and Vitamin D Supplementation

- Instruct patients being treated for Paget’s disease of bone on the importance of calcium and vitamin D supplementation in maintaining serum calcium levels, and on the symptoms of hypocalcemia. All patients should take 1500 mg elemental calcium daily in divided doses (750 mg two times a day, or 500 mg three times a day) and 800 international units vitamin D daily, particularly in the 2 weeks following zoledronic acid injection administration [see Warnings and Precautions (5.2)].

2.9 Method of Administration

The zoledronic acid infusion time must not be less than 15 minutes given over a constant infusion rate.

The i.v. infusion should be followed by a 10 mL normal saline flush of the intravenous line.

Zoledronic acid injection solution for infusion must not be allowed to come in contact with any calcium or other divalent cation-containing solutions, and should be administered as a single intravenous solution through a separate vented infusion line.

If refrigerated, allow the refrigerated solution to reach room temperature before administration. After opening, the solution is stable for 24 hours at 2° to 8°C (36° to 46°F) [see How Supplied/Storage and Handling (16)].

3 DOSAGE FORMS AND STRENGTHS

5 mg in a 100 mL ready to infuse solution.

4 CONTRAINDICATIONS

Zoledronic acid is contraindicated in patients with the following conditions:

- Hypocalcemia [see Warnings and Precautions (5.2)]
- Creatinine clearance less than 35 mL/min and in those with evidence of acute renal impairment due to an increased risk of renal failure [see Warnings and Precautions (5.3)].
- Known hypersensitivity to zoledronic acid or any components of zoledronic acid injection. Hypersensitivity reactions including urticaria, angioedema, and anaphylactic reaction/shock have been reported [see Adverse Reactions (6.2)].

5 WARNINGS AND PRECAUTIONS

5.1 Drug Products with Same Active Ingredient

Zoledronic acid contains the same active ingredient found in Zometa, used for oncology indications, and a patient being treated with Zometa should not be treated with zoledronic acid.

5.2 Hypocalcemia and Mineral Metabolism

Pre-existing hypocalcemia and disturbances of mineral metabolism (e.g., hypoparathyroidism, thyroid surgery, parathyroid surgery; malabsorption syndromes, excision of small intestine) must be effectively treated before initiating therapy with zoledronic acid. Clinical monitoring of calcium and mineral levels (phosphorus and magnesium) is highly recommended for these patients [see Contraindications (4)].

Hypocalcemia following zoledronic acid administration is a significant risk in Paget’s disease. All patients should be instructed about the symptoms of hypocalcemia and the importance of calcium and vitamin D supplementation in maintaining serum calcium levels [see Dosage and Administration (2.8), Adverse Reactions (6.1), Patient Counseling Information (17)].

5.3 Renal Impairment

A single dose of zoledronic acid should not exceed 5 mg and the duration of infusion should be no less than 15 minutes [see Dosage and Administration (2)].

Zoledronic acid is contraindicated in patients with creatinine clearance less than 35 mL/min and in those with evidence of acute renal impairment [see Contraindications (4)]. If history or physical signs suggest dehydration, zoledronic acid therapy should be withheld until normovolemic status has been achieved [see Adverse Reactions (6.2)].

Zoledronic acid should be used with caution in patients with chronic renal impairment. Acute renal impairment, including renal failure, has been observed following the administration of zoledronic acid, especially in patients with pre-existing renal compromise, advanced age, concomitant nephrotoxic medications, concomitant diuretic therapy, or severe dehydration occurring before or after zoledronic acid administration. Acute renal failure (ARF) has been observed in patients after a single administration. Rare reports of hospitalization and/or dialysis or fatal outcome occurred in patients with underlying moderate to severe renal impairment or with any of the risk factors described in this section [see Adverse Reactions (6.2)]. Renal impairment may lead to increased exposure of concomitant medications and/or their metabolites that are primarily renally excreted [see Drug Interactions (7.4)].

Creatinine clearance should be calculated based on actual body weight using Cockcroft-Gault formula before each zoledronic acid dose. Transient increase in serum creatinine may be greater in patients with impaired renal function; interim monitoring of creatinine clearance should be performed in at-risk patients. Elderly patients and those receiving diuretic therapy are at increased risk of acute renal failure. These patients should have their fluid status assessed and be appropriately hydrated prior to administration of zoledronic acid. Zoledronic acid should be used with caution with other nephrotoxic drugs [see Drug Interactions (7.3)]. Consider monitoring creatinine clearance in patients at-risk for ARF who are taking concomitant medications that are primarily excreted by the kidney [see Drug Interactions (7.4)].

5.4 Osteonecrosis of the Jaw

Osteonecrosis of the jaw (ONJ) has been reported in patients treated with bisphosphonates, including zoledronic acid. Most cases have been in cancer patients treated with intravenous bisphosphonates undergoing dental procedures. A routine oral examination should be performed by the prescriber prior to initiation of bisphosphonate treatment. A dental examination with appropriate preventive dentistry should be considered prior to treatment with bisphosphonates in patients with a history of concomitant risk factors (e.g., cancer, chemotherapy, angiogenesis inhibitors, radiotherapy, corticosteroids, poor oral hygiene, pre-existing dental disease or infection, anemia, coagulopathy). The risk of ONJ may increase with duration of exposure to bisphosphonates. Concomitant administration of drugs associated with ONJ may increase the risk of developing ONJ.

While on treatment, patients with concomitant risk factors should avoid invasive dental procedures if possible. For patients who develop ONJ while on bisphosphonate therapy, dental surgery may exacerbate the condition. For patients requiring dental procedures, there are no data available to suggest whether discontinuation of bisphosphonate treatment reduces the risk of ONJ. The clinical judgment of the treating physician should guide the management plan of each patient based on individual benefit/risk assessment [see Adverse Reactions (6.1)].

5.5 Atypical Subtrochanteric and Diaphyseal Femoral Fractures

Atypical, low-energy, or low trauma fractures of the femoral shaft have been reported in bisphosphonate-treated patients. These fractures can occur anywhere in the femoral shaft from just below the lesser trochanter to above the supracondylar flare and are transverse or short oblique in orientation without evidence of comminution.

Atypical femur fractures most commonly occur with minimal or no trauma to the affected area. They may be bilateral and many patients report prodromal pain in the affected area, usually presenting as dull, aching thigh pain, weeks to months before a complete fracture occurs.

Any patient with a history of bisphosphonate exposure who presents with thigh or groin pain should be suspected of having an atypical fracture and should be evaluated to rule out an incomplete femur fracture. Patients presenting with an atypical femur fracture should also be assessed for symptoms and signs of fracture in the contralateral limb. Interruption of bisphosphonate therapy should be considered, pending a risk/benefit assessment, on an individual basis.

5.6 Musculoskeletal Pain

In post-marketing experience, severe and occasionally incapacitating bone, joint, and/or muscle pain have been infrequently reported in patients taking bisphosphonates, including zoledronic acid. The time to onset of symptoms varied from one day to several months after starting the drug. Consider withholding future zoledronic acid treatment if severe symptoms develop. Most patients had relief of symptoms after stopping. A subset had recurrence of symptoms when rechallenged with the same drug or another bisphosphonate [see Adverse Reactions (6.2)].

5.7 Patients with Asthma

While not observed in clinical trials with zoledronic acid, there have been reports of bronchoconstriction in aspirin-sensitive patients receiving bisphosphonates. Use zoledronic acid with caution in aspirin-sensitive patients.

6 ADVERSE REACTIONS

6.1 Clinical Trials Experience

Because clinical trials are conducted under widely varying conditions, adverse reaction rates observed in the clinical trials of a drug cannot be directly compared to rates in the clinical trials of another drug and may not reflect the rates observed in practice.

Paget’s Disease of Bone

In the Paget’s disease trials, two 6-month, double-blind, comparative, multinational studies of 349 men and women aged greater than 30 years with moderate to severe disease and with confirmed Paget’s disease of bone, 177 patients were exposed to zoledronic acid and 172 patients exposed to risedronate. Zoledronic acid was administered once as a single 5 mg dose in 100 mL solution infused over at least 15 minutes. Risedronate was given as an oral daily dose of 30 mg for 2 months.

The incidence of serious adverse events was 5.1% in the zoledronic acid group and 6.4% in the risedronate group. The percentage of patients who withdrew from the study due to adverse events was 1.7% and 1.2% for the zoledronic acid and risedronate groups, respectively.

Adverse reactions occurring in at least 2% of the Paget’s patients receiving zoledronic acid (single 5 mg intravenous infusion) or risedronate (30 mg oral daily dose for 2 months) over a 6-month study period are listed by system organ class in Table 4.

Table 4. Adverse Reactions Reported in at Least 2% of Paget’s Patients Receiving Zoledronic Acid (Single 5 mg Intravenous Infusion) or Risedronate (Oral 30 mg Daily for 2 Months) Over a 6-Month Follow-Up Period
System Organ Class | 5 mg IV zoledronic acid % (N = 177) | 30 mg/day x 2 Months risedronate % (N = 172)
Infections and Infestations
Influenza | 7 | 5
Metabolism and Nutrition Disorders
Hypocalcemia | 3 | 1
Anorexia | 2 | 2
Nervous System Disorders
Headache | 11 | 10
Dizziness | 9 | 4
Lethargy | 5 | 1
Paresthesia | 2 | 0
Respiratory, Thoracic and Mediastinal Disorders
Dyspnea | 5 | 1
Gastrointestinal Disorders
Nausea | 9 | 6
Diarrhea | 6 | 6
Constipation | 6 | 5
Dyspepsia | 5 | 4
Abdominal Distension | 2 | 1
Abdominal Pain | 2 | 2
Vomiting | 2 | 2
Abdominal Pain Upper | 1 | 2
Skin and Subcutaneous Tissue Disorders
Rash | 3 | 2
Musculoskeletal, Connective Tissue and Bone Disorders
Arthralgia | 9 | 11
Bone Pain | 9 | 5
Myalgia | 7 | 4
Back Pain | 4 | 7
Musculoskeletal Stiffness | 2 | 1
General Disorders and Administrative Site Conditions
Influenza-like Illness | 11 | 6
Pyrexia | 9 | 2
Fatigue | 8 | 4
Rigors | 8 | 1
Pain | 5 | 4
Peripheral Edema | 3 | 1
Asthenia | 2 | 1

Laboratory Findings

In the Paget’s disease trials, early, transient decreases in serum calcium and phosphate levels were observed. Approximately 21% of patients had serum calcium levels less than 8.4 mg/dL 9 to 11 days following zoledronic acid administration.

Renal Impairment

In clinical trials in Paget’s disease there were no cases of renal deterioration following a single 5 mg 15-minute infusion [see Warnings and Precautions (5.3)].

Acute Phase Reaction

The signs and symptoms of acute phase reaction (influenza-like illness, pyrexia, myalgia, arthralgia, and bone pain) were reported in 25% of patients in the zoledronic acid-treated group compared to 8% in the risedronate-treated group. Symptoms usually occur within the first 3 days following zoledronic acid administration. The majority of these symptoms resolved within 4 days of onset.

Osteonecrosis of the Jaw

Osteonecrosis of the jaw has been reported with zoledronic acid [see Warnings and Precautions (5.4)].

6.2 Post-Marketing Experience

Because these reactions are reported voluntarily from a population of uncertain size, it is not always possible to reliably estimate their frequency or establish a causal relationship to drug exposure.

The following adverse reactions have been identified during post approval use of zoledronic acid:

Acute Phase Reactions

Fever, headache, flu-like symptoms, nausea, vomiting, diarrhea, arthralgia, and myalgia. Symptoms may be significant and lead to dehydration.

Acute Renal Failure

Acute renal failure requiring hospitalization and/or dialysis or with a fatal outcome have been rarely reported. Increased serum creatinine was reported in patients with 1) underlying renal disease, 2) dehydration secondary to fever, sepsis, gastrointestinal losses, or diuretic therapy, or 3) other risk factors such as advanced age, or concomitant nephrotoxic drugs in the post-infusion period. Transient rise in serum creatinine can be correctable with intravenous fluids.

Allergic Reactions

Allergic reactions with intravenous zoledronic acid including anaphylactic reaction/shock, urticaria, angioedema, Stevens-Johnson syndrome, toxic epidermal necrolysis, and bronchoconstriction have been reported.

Asthma Exacerbations

Asthma exacerbations have been reported.

Hypocalcemia

Hypocalcemia has been reported.

Hypophosphatemia

Hypophosphatemia has been reported.

Osteonecrosis of the Jaw

Osteonecrosis of the jaw has been reported.

Osteonecrosis of other bones

Cases of osteonecrosis of other bones (including femur, hip, knee, ankle, wrist and humerus) have been reported; causality has not been determined in the population treated with zoledronic acid.

Ocular Adverse Events

Cases of the following events have been reported: conjunctivitis, iritis, iridocyclitis, uveitis, episcleritis, scleritis and orbital inflammation/edema.

Other

Hypotension in patients with underlying risk factors has been reported.

7 DRUG INTERACTIONS

No in vivo drug interaction studies have been performed for zoledronic acid. In vitro and ex vivo studies showed low affinity of zoledronic acid for the cellular components of human blood. In vitro mean zoledronic acid protein binding in human plasma ranged from 28% at 200 ng/mL to 53% at 50 ng/mL. In vivo studies showed that zoledronic acid is not metabolized, and is excreted into the urine as the intact drug.

7.1 Aminoglycosides

Caution is advised when bisphosphonates, including zoledronic acid, are administered with aminoglycosides, since these agents may have an additive effect to lower serum calcium level for prolonged periods. This effect has not been reported in zoledronic acid clinical trials.

7.2 Loop Diuretics

Caution should also be exercised when zoledronic acid is used in combination with loop diuretics due to an increased risk of hypocalcemia.

7.3 Nephrotoxic Drugs

Caution is indicated when zoledronic acid is used with other potentially nephrotoxic drugs such as nonsteroidal anti-inflammatory drugs.

7.4 Drugs Primarily Excreted by the Kidney

Renal impairment has been observed following the administration of zoledronic acid in patients with pre-existing renal compromise or other risk factors [see Warnings and Precautions (5.3)]. In patients with renal impairment, the exposure to concomitant medications that are primarily renally excreted (e.g., digoxin) may increase. Consider monitoring serum creatinine in patients at risk for renal impairment who are taking concomitant medications that are primarily excreted by the kidney.

8 USE IN SPECIFIC POPULATIONS

8.1 Pregnancy

Risk Summary

Available data on the use of zoledronic acid in pregnant women are insufficient to inform a drug-associated risk of adverse maternal or fetal outcomes. Discontinue zoledronic acid when pregnancy is recognized.

In animal reproduction studies, daily subcutaneous administration of zoledronic acid to pregnant rats during organogenesis resulted in increases in fetal skeletal, visceral, and external malformations, decreases in post-implantation survival, and decreases in viable fetuses and fetal weight starting at doses equivalent to 2 times the recommended human 5 mg intravenous dose (based on AUC). Subcutaneous administration of zoledronic acid to rabbits during organogenesis did not cause adverse fetal effects at up to 0.4 times the human 5 mg intravenous dose (based on body surface area, mg/m2), but resulted in maternal mortality and abortion associated with hypocalcemia starting at doses equivalent to 0.04 times the human 5 mg intravenous dose. Subcutaneous dosing of female rats from before mating through gestation and lactation and allowed to deliver caused maternal dystocia and periparturient mortality, increases in stillbirths and neonatal deaths, and reduced pup body weight starting at doses equivalent to 0.1 times the human 5 mg intravenous dose (based on AUC). (see Data).

Bisphosphonates are incorporated into the bone matrix, from which they are gradually released over a period of years. The amount of bisphosphonate incorporated into adult bone, and available for release into the systemic circulation is directly related to the dose and duration of bisphosphonate use. Consequently, based on the mechanism of action of bisphosphonates, there is a potential risk of fetal harm, predominantly skeletal, if a woman becomes pregnant after completing a course of bisphosphonate therapy. The impact of variables such as time between cessation of bisphosphonate therapy to conception, the particular bisphosphonate used, and the route of administration (intravenous versus oral) on the risk has not been studied.

The estimated background risk of major birth defects and miscarriage for the indicated populations is unknown. All pregnancies have a background risk of birth defects, loss, or other adverse outcomes. In the U.S. general population, the estimated background risks of major birth defects and miscarriage in clinically recognized pregnancies is 2 to 4% and 15 to 20%, respectively.

Data

Animal Data

In pregnant rats given daily subcutaneous doses of zoledronic acid of 0.1, 0.2, or 0.4 mg/kg during organogenesis, fetal skeletal, visceral, and external malformations, increases in pre- and post-implantation loss, and decreases in viable fetuses and fetal weight were observed at 0.2 and 0.4 mg/kg/day (equivalent to 2 and 4 times the human 5 mg intravenous dose, based on AUC). Adverse fetal skeletal effects at 0.4 mg/kg/day (4 times the human 5 mg dose) included unossified or incompletely ossified bones, thickened, curved or shortened bones, wavy ribs, and shortened jaw. Other adverse fetal effects at this dose included reduced lens, rudimentary cerebellum, reduction or absence of liver lobes, reduction of lung lobes, vessel dilation, cleft palate, and edema. Skeletal variations were observed in all groups starting at 0.1 mg/kg/day (1.2 times the human 5 mg dose). Signs of maternal toxicity including reduced body weight and food consumption were observed at 0.4 mg/kg/day (4 times the human 5 mg dose).

In pregnant rabbits given daily subcutaneous doses of zoledronic acid of 0.01, 0.03, or 0.1 mg/kg during gestation no adverse fetal effects were observed up to 0.1 mg/kg/day (0.4 times the human 5 mg intravenous dose, based on body surface area, mg/m2). Maternal mortality and abortion were observed in all dose groups (starting at 0.04 times the human 5 mg dose). Adverse maternal effects were associated with drug-induced hypocalcemia.

In female rats given daily subcutaneous doses of 0.01, 0.03, or 0.1 mg/kg, beginning 15 days before mating and continuing through gestation, parturition and lactation, dystocia and periparturient mortality were observed in pregnant rats allowed to deliver starting at 0.01 mg/kg/day (0.1 times the human 5 mg intravenous dose, based on AUC). Also, there was an increase in stillbirths and a decrease in neonate survival starting at 0.03 mg/kg/day (0.3 times the human 5 mg dose), while the number of viable newborns and pup body weight on postnatal Day 7 were decreased at 0.1 mg/kg/day (equivalent to the human 5 mg dose). Maternal and neonatal deaths were considered related to drug-induced periparturient hypocalcemia.

8.2 Lactation

Risk Summary

There are no data on the presence of zoledronic acid in human milk, the effects on the breastfed infant, or the effects on milk production. The developmental and health benefits of breast-feeding should be considered along with the mother’s clinical need for zoledronic acid and any potential adverse effects on the breast-fed child from zoledronic acid or from the underlying maternal condition.

8.3 Females and Males of Reproductive Potential

Infertility

There are no data available in humans. Female fertility may be impaired based on animal studies demonstrating adverse effects of zoledronic acid on fertility parameters [see Nonclinical Toxicology (13.1)].

8.4 Pediatric Use

Zoledronic acid is not indicated for use in children.

The safety and effectiveness of zoledronic acid was studied in a one-year active controlled trial of 152 pediatric subjects (74 receiving zoledronic acid). The enrolled population was subjects with severe osteogenesis imperfecta, aged 1 to 17 years, 55% male, 84% Caucasian, with a mean lumbar spine BMD of 0.431 gm/cm^2, which is 2.7 standard deviations below the mean for age-matched controls (BMD Z-score of -2.7). At one year, increases in BMD were observed in the zoledronic acid treatment group. However, changes in BMD in individual patients with severe osteogenesis imperfecta did not necessarily correlate with the risk for fracture or the incidence or severity of chronic bone pain. The adverse events observed with zoledronic acid use in children did not raise any new safety findings beyond those previously seen in adults treated for Paget’s disease of bone including osteonecrosis of the jaw (ONJ) and renal impairment. However, adverse reactions seen more commonly in pediatric patients included pyrexia (61%), arthralgia (26%), hypocalcemia (22%) and headache (22%). These reactions, excluding arthralgia, occurred most frequently within three days after the first infusion and became less common with repeat dosing. No cases of ONJ or renal impairment were observed in this study. Because of long-term retention in bone, zoledronic acid should only be used in children if the potential benefit outweighs the potential risk.

Plasma zoledronic acid concentration data was obtained from 10 patients with severe osteogenesis imperfecta (4 in the age group of 3 to 8 years and 6 in the age group of 9 to 17 years) infused with 0.05 mg/kg dose over 30 minutes. Mean Cmax and AUC(0-last) was 167 ng/mL and 220 ng.h/mL respectively. The plasma concentration time profile of zoledronic acid in pediatric patients represent a multi-exponential decline, as observed in adult cancer patients at an approximately equivalent mg/kg dose.

8.5 Geriatric Use

Of the patients receiving zoledronic acid in the Paget’s disease studies, 132 patients, were 65 years of age or over, while 68 patients, were at least 75 years of age.

Because decreased renal function occurs more commonly in the elderly, special care should be taken to monitor renal function.

8.6 Renal Impairment

Zoledronic acid is contraindicated in patients with creatinine clearance less than 35 mL/min and in those with evidence of acute renal impairment. There are no safety or efficacy data to support the adjustment of the zoledronic acid dose based on baseline renal function. Therefore, no dosage adjustment is required in patients with a creatinine clearance of greater than or equal to 35 mL/min [see Warnings and Precautions (5.3), Clinical Pharmacology (12.3)]. Risk of acute renal failure may increase with underlying renal disease and dehydration secondary to fever, sepsis, gastrointestinal losses, diuretic therapy, advanced age, etc. [see Adverse Reactions (6.2)].

8.7 Hepatic Impairment

Zoledronic acid is not metabolized in the liver. No clinical data are available for use of zoledronic acid in patients with hepatic impairment.

10 OVERDOSAGE

Clinical experience with acute overdosage of zoledronic acid solution for intravenous infusion is limited. Patients who have received doses higher than those recommended should be carefully monitored. Overdosage may cause clinically significant renal impairment, hypocalcemia, hypophosphatemia, and hypomagnesemia. Clinically relevant reductions in serum levels of calcium, phosphorus, and magnesium should be corrected by intravenous administration of calcium gluconate, potassium or sodium phosphate, and magnesium sulfate, respectively.

Single doses of zoledronic acid should not exceed 5 mg and the duration of the intravenous infusion should be no less than 15 minutes [see Dosage and Administration (2)].

11 DESCRIPTION

Zoledronic acid injection contains zoledronic acid, a bisphosphonic acid which is an inhibitor of osteoclastic bone resorption. Zoledronic acid, USP is designated chemically as (1-Hydroxy-2-imidazol-1-yl-ethylidene) diphosphonic acid, monohydrate and its structural formula is:

Zoledronic acid monohydrate is a white crystalline powder. Its molecular formula is C5H10N2O7P2 • H2O and a molar mass of 290.1 g/Mol. Zoledronic acid monohydrate is highly soluble in 0.1N sodium hydroxide solution, sparingly soluble in water and 0.1N hydrochloric acid, and practically insoluble in organic solvents. The pH of the zoledronic acid injection solution for infusion is approximately 6.0 to 7.0.

Zoledronic acid injection is available as a sterile solution in vial for intravenous infusion. One vial with 100 mL solution contains 5.330 mg of zoledronic acid monohydrate, equivalent to 5 mg zoledronic acid, USP on an anhydrous basis.

Inactive Ingredients: 4950 mg of mannitol, USP; and 30 mg of sodium citrate, USP.

12 CLINICAL PHARMACOLOGY

12.1 Mechanism of Action

Zoledronic acid is a bisphosphonate and acts primarily on bone. It is an inhibitor of osteoclast-mediated bone resorption.

The selective action of bisphosphonates on bone is based on their high affinity for mineralized bone. Intravenously administered zoledronic acid rapidly partitions to bone and localizes preferentially at sites of high bone turnover. The main molecular target of zoledronic acid in the osteoclast is the enzyme farnesyl pyrophosphate synthase. The relatively long duration of action of zoledronic acid is attributable to its high binding affinity to bone mineral.

12.3 Pharmacokinetics

Pharmacokinetic data in patients with Paget’s disease of bone are not available.

Distribution

Single or multiple (every 28 days) 5-minute or 15-minute infusions of 2, 4, 8 or 16 mg zoledronic acid were given to 64 patients with cancer and bone metastases. The post-infusion decline of zoledronic acid concentrations in plasma was consistent with a triphasic process showing a rapid decrease from peak concentrations at end-of-infusion to less than 1% of Cmax 24 hours post infusion with population half-lives of t1/2α 0.24 hour and t1/2β 1.87 hours for the early disposition phases of the drug. The terminal elimination phase of zoledronic acid was prolonged, with very low concentrations in plasma between Days 2 and 28 post infusion, and a terminal elimination half-life t1/2γ of 146 hours. The area under the plasma concentration versus time curve (AUC0-24h) of zoledronic acid was dose proportional from 2 to 16 mg. The accumulation of zoledronic acid measured over three cycles was low, with mean AUC0-24h ratios for cycles 2 and 3 versus 1 of 1.13 ± 0.30 and 1.16 ± 0.36, respectively.

In vitro and ex vivo studies showed low affinity of zoledronic acid for the cellular components of human blood. In vitro mean zoledronic acid protein binding in human plasma ranged from 28% at 200 ng/mL to 53% at 50 ng/mL.

Metabolism

Zoledronic acid does not inhibit human P450 enzymes in vitro. Zoledronic acid does not undergo biotransformation in vivo. In animal studies, less than 3% of the administered intravenous dose was found in the feces, with the balance either recovered in the urine or taken up by bone, indicating that the drug is eliminated intact via the kidney. Following an intravenous dose of 20 nCi 14C-zoledronic acid in a patient with cancer and bone metastases, only a single radioactive species with chromatographic properties identical to those of parent drug was recovered in urine, which suggests that zoledronic acid is not metabolized.

Excretion

In 64 patients with cancer and bone metastases on average (± SD) 39 ± 16% of the administered zoledronic acid dose was recovered in the urine within 24 hours, with only trace amounts of drug found in urine post Day 2. The cumulative percent of drug excreted in the urine over 0 to 24 hours was independent of dose. The balance of drug not recovered in urine over 0 to 24 hours, representing drug presumably bound to bone, is slowly released back into the systemic circulation, giving rise to the observed prolonged low plasma concentrations. The 0 to 24 hour renal clearance of zoledronic acid was 3.7 ± 2.0 L/h.

Zoledronic acid clearance was independent of dose but dependent upon the patient’s creatinine clearance. In a study in patients with cancer and bone metastases, increasing the infusion time of a 4 mg dose of zoledronic acid from 5 minutes (n = 5) to 15 minutes (n = 7) resulted in a 34% decrease in the zoledronic acid concentration at the end of the infusion ([mean ± SD] 403 ± 118 ng/mL vs. 264 ± 86 ng/mL) and a 10% increase in the total AUC (378 ± 116 ng x h/mL vs. 420 ± 218 ng x h/mL). The difference between the AUC means was not statistically significant.

Specific Populations

Pediatrics

Zoledronic acid is not indicated for use in children [see Pediatric Use (8.4)].

Geriatrics

The pharmacokinetics of zoledronic acid was not affected by age in patients with cancer and bone metastases whose age ranged from 38 years to 84 years.

Race

The pharmacokinetics of zoledronic acid was not affected by race in patients with cancer and bone metastases.

Hepatic Impairment

No clinical studies were conducted to evaluate the effect of hepatic impairment on the pharmacokinetics of zoledronic acid.

Renal Impairment

The pharmacokinetic studies conducted in 64 cancer patients represented typical clinical populations with normal to moderately-impaired renal function. Compared to patients with creatinine clearance greater than 80 mL/min (N = 37), patients with creatinine clearance = 50 to 80 mL/min (N = 15) showed an average increase in plasma AUC of 15%, whereas patients with creatinine clearance = 30 to 50 mL/min (N = 11) showed an average increase in plasma AUC of 43%. No dosage adjustment is required in patients with a creatinine clearance of greater than or equal to 35 mL/min. Zoledronic acid is contraindicated in patients with creatinine clearance less than 35 mL/min and in those with evidence of acute renal impairment due to an increased risk of renal failure [see Contraindications (4), Warnings and Precautions (5.3), Use in Specific Populations (8.6)].

13 NONCLINICAL TOXICOLOGY

13.1 Carcinogenesis, Mutagenesis, Impairment of Fertility

Carcinogenesis

Lifetime carcinogenicity bioassays were conducted in mice and rats. Mice were given daily oral doses of zoledronic acid of 0.1, 0.5, or 2.0 mg/kg/day for 2 years. There was an increased incidence of Harderian gland adenomas in males and females in all treatment groups (starting at doses equivalent to 0.002 times the human 5 mg intravenous dose, based on body surface area, mg/m2). Rats were given daily oral doses of zoledronic acid of 0.1, 0.5, or 2.0 mg/kg/day for 2 years. No increased incidence of tumors was observed at any dose (up to 0.1 times the human intravenous dose of 5 mg, based on body surface area, mg/m2).

Mutagenesis

Zoledronic acid was not genotoxic in the Ames bacterial mutagenicity assay, in the Chinese hamster ovary cell assay, or in the Chinese hamster gene mutation assay, with or without metabolic activation. Zoledronic acid was not genotoxic in the in vivo rat micronucleus assay.

Impairment of Fertility

Female rats were given daily subcutaneous doses of zoledronic acid of 0.01, 0.03, or 0.1 mg/kg beginning 15 days before mating and continuing through gestation. Inhibition of ovulation and a decrease in the number of pregnant rats were observed at 0.1 mg/kg/day (equivalent to the human 5 mg intravenous dose, based on AUC). An increase in preimplantation loss and a decrease in the number of implantations and live fetuses were observed at 0.03 and 1 mg/kg/day (0.3 to 1 times the human 5 mg human intravenous dose).

13.2 Animal Toxicology and/or Pharmacology

Bone Safety Studies

Zoledronic acid is a potent inhibitor of osteoclastic bone resorption. In the ovariectomized rat, single IV doses of zoledronic acid of 4 to 500 mcg/kg (0.1 to 3.5 times the human 5 mg intravenous dose, based on body surface area, mg/m2) suppressed bone turnover and protected against trabecular bone loss, cortical thinning and the reduction in vertebral and femoral bone strength in a dose-dependent manner. At a dose equivalent to human exposure at the 5 mg intravenous dose, the effect persisted for 8 months, which corresponds to approximately 8 remodeling cycles or 3 years in humans.

In ovariectomized rats and monkeys, weekly treatment with zoledronic acid dose-dependently suppressed bone turnover and prevented the decrease in cancellous and cortical BMD and bone strength, at yearly cumulative doses up to 3.5 times the human 5 mg intravenous dose, based on body surface area, mg/m2. Bone tissue was normal and there was no evidence of a mineralization defect, no accumulation of osteoid, and no woven bone.

14 CLINICAL STUDIES

14.5 Treatment of Paget’s Disease of Bone

Zoledronic acid was studied in male and female patients with moderate to severe Paget’s disease of bone, defined as serum alkaline phosphatase level at least twice the upper limit of the age-specific normal reference range at the time of study entry. Diagnosis was confirmed by radiographic evidence.

The efficacy of one infusion of 5 mg zoledronic acid vs. oral daily doses of 30 mg risedronate for 2 months was demonstrated in two identically designed 6-month randomized, double-blind trials. The mean age of patients in the two trials was 70. Ninety-three percent (93%) of patients were Caucasian. Therapeutic response was defined as either normalization of serum alkaline phosphatase (SAP) or a reduction of at least 75% from baseline in total SAP excess at the end of 6 months. SAP excess was defined as the difference between the measured level and midpoint of normal range.

In both trials zoledronic acid demonstrated a superior and more rapid therapeutic response compared with risedronate and returned more patients to normal levels of bone turnover, as evidenced by biochemical markers of formation (SAP, serum N-terminal propeptide of type I collagen [P1NP]) and resorption (serum CTx 1 [cross-linked C-telopeptides of type I collagen] and urine α-CTx).

The 6-month combined data from both trials showed that 96% (169/176) of zoledronic acid-treated patients achieved a therapeutic response as compared with 74% (127/171) of patients treated with risedronate. Most zoledronic acid patients achieved a therapeutic response by the Day 63 visit. In addition, at 6 months, 89% (156/176) of zoledronic acid-treated patients achieved normalization of SAP levels, compared to 58% (99/171) of patients treated with risedronate (p<0.0001) (see Figure 2).

Figure 2. Therapeutic Response/Serum Alkaline Phosphatase (SAP) Normalization Over Time

The therapeutic response to zoledronic acid was similar across demographic and disease-severity groups defined by gender, age, previous bisphosphonate use, and disease severity. At 6 months, the percentage of zoledronic acid-treated patients who achieved therapeutic response was 97% and 95%, respectively, in each of the baseline disease severity subgroups (baseline SAP less than 3xULN, greater than or equal to 3xULN) compared to 75% and 74%, respectively, for the same disease severity subgroups of risedronate-treated patients.

In patients who had previously received treatment with oral bisphosphonates, therapeutic response rates were 96% and 55% for zoledronic acid and risedronate, respectively. The comparatively low risedronate response was due to the low response rate (7/23, 30%) in patients previously treated with risedronate. In patients naïve to previous treatment, a greater therapeutic response was also observed with zoledronic acid (98%) relative to risedronate (86%). In patients with symptomatic pain at screening, therapeutic response rates were 94% and 70% for zoledronic acid and risedronate respectively. For patients without pain at screening, therapeutic response rates were 100% and 82% for zoledronic acid and risedronate respectively.

Bone histology was evaluated in 7 patients with Paget’s disease 6 months after being treated with zoledronic acid 5 mg. Bone biopsy results showed bone of normal quality with no evidence of impaired bone remodeling and no evidence of mineralization defect.

16 HOW SUPPLIED/STORAGE AND HANDLING

Zoledronic acid injection is supplied as follow:

Each vial contains 5 mg/100 mL. NDC 67457-619-10

Handling

After opening the solution, it is stable for 24 hours at 2° to 8°C (36° to 46°F).

If refrigerated, allow the refrigerated solution to reach room temperature before administration.

Storage

Store at 20° to 25°C (68° to 77°F); excursions permitted between 15º to 30°C (59° to 86°F). [See USP Controlled Room Temperature.]

17 PATIENT COUNSELING INFORMATION

Advise the patient to read the FDA-approved patient labeling (Medication Guide).

Information for Patients

Patients should be made aware that zoledronic acid contains the same active ingredient (zoledronic acid) found in Zometa®, and that patients being treated with Zometa should not be treated with zoledronic acid.

Zoledronic acid is contraindicated in patients with creatinine clearance less than 35 mL/min [see Contraindications (4)].

Before being given zoledronic acid, patients should tell their doctor if they have kidney problems and what medications they are taking.

Zoledronic acid should not be given if the patient is pregnant or plans to become pregnant, or if she is breast-feeding [see Warnings and Precautions (5.6)].

There have been reports of bronchoconstriction in aspirin-sensitive patients receiving bisphosphonates, including zoledronic acid. Before being given zoledronic acid, patients should tell their doctor if they are aspirin-sensitive.

If the patient had surgery to remove some or all of the parathyroid glands in their neck, or had sections of their intestine removed, or are unable to take calcium supplements they should tell their doctor.

Zoledronic acid is given as an infusion into a vein by a nurse or a doctor, and the infusion time must not be less than 15 minutes.

On the day of treatment the patient should eat and drink normally, which includes drinking at least 2 glasses of fluid such as water within a few hours prior to the infusion, as directed by their doctor, before receiving zoledronic acid.

After getting zoledronic acid it is strongly recommended patients with Paget’s disease take calcium in divided doses (for example, 2 to 4 times a day) for a total of 1500 mg calcium a day to prevent low blood calcium levels. This is especially important for the two weeks after getting zoledronic acid [see Warnings and Precautions (5.2)].

Patients should be aware of the most commonly associated side effects of therapy. Patients may experience one or more side effects that could include: fever, flu-like symptoms, myalgia, arthralgia, and headache. Most of these side effects occur within the first 3 days following the dose of zoledronic acid. They usually resolve within 3 days of onset but may last for up to 7 to 14 days. Patients should consult their physician if they have questions or if these symptoms persist. The incidence of these symptoms decreased markedly with subsequent doses of zoledronic acid.

Administration of acetaminophen following zoledronic acid administration may reduce the incidence of these symptoms.

Physicians should inform their patients that there have been reports of persistent pain and/or a non-healing sore of the mouth or jaw, primarily in patients treated with bisphosphonates for other illnesses. During treatment with zoledronic acid, patients should be instructed to maintain good oral hygiene and undergo routine dental check-ups. If they experience any oral symptoms, they should immediately report them to their physician or dentist.

Severe and occasionally incapacitating bone, joint, and/or muscle pain have been infrequently reported in patients taking bisphosphonates, including zoledronic acid. Consider withholding future zoledronic acid treatment if severe symptoms develop.

Atypical femur fractures in patients on bisphosphonate therapy have been reported; patients with thigh or groin pain should be evaluated to rule out a femoral fracture.

Zometa® is a trademark of Novartis.

Manufactured for:
Mylan Institutional LLC
Morgantown, WV 26505 U.S.A.

Manufactured by:
Mylan Laboratories Limited
Bangalore, India

1034712

OCTOBER 2023

Medication Guide

Zoledronic Acid
(ZOE-le-DRON-ik AS-id) Injection

Read the Medication Guide that comes with zoledronic acid injection before you start taking it and each time you get a refill. There may be new information. This Medication Guide does not take the place of talking with your doctor about your medical condition or treatment. Talk to your doctor if you have any questions about zoledronic acid injection.

What is the most important information I should know about zoledronic acid injection?

You should not receive zoledronic acid injection if you are already receiving Zometa. Both zoledronic acid injection and Zometa contain zoledronic acid.

Zoledronic acid injection can cause serious side effects including:

1. Low calcium levels in your blood (hypocalcemia)
2. Severe kidney problems
3. Severe jaw bone problems (osteonecrosis)
4. Unusual thigh bone fractures
5. Bone, joint or muscle pain
1. Low calcium levels in your blood (hypocalcemia).

Zoledronic acid injection may lower the calcium levels in your blood. If you have low blood calcium before you start taking zoledronic acid injection, it may get worse during treatment. Your low blood calcium must be treated before you take zoledronic acid injection. Most people with low blood calcium levels do not have symptoms, but some people may have symptoms. Call your doctor right away if you have symptoms of low blood calcium such as:

- Spasms, twitches, or cramps in your muscles
- Numbness or tingling in your fingers, toes, or around your mouth

Your doctor may prescribe calcium and vitamin D to help prevent low calcium levels in your blood, while you take zoledronic acid injection. Take calcium and vitamin D as your doctor tells you to.

2. Severe kidney problems.

Severe kidney problems may happen when you take zoledronic acid injection. Severe kidney problems may lead to hospitalization or kidney dialysis and can be life-threatening. Your risk of kidney problems is higher if you:

- already have kidney problems
- take a diuretic or “water pill”
- do not have enough water in your body (dehydrated) before or after you receive zoledronic acid injection
- are of advanced age since the risk increases as you get older
- take any medicines known to harm your kidneys

You should drink at least 2 glasses of fluid within a few hours before receiving zoledronic acid injection to reduce the risk of kidney problems.

3. Severe jaw bone problems (osteonecrosis).

Severe jaw bone problems may happen when you take zoledronic acid injection. Your doctor should examine your mouth before you start zoledronic acid injection. Your doctor may tell you to see your dentist before you start zoledronic acid injection. It is important for you to practice good mouth care during treatment with zoledronic acid injection.

4. Unusual thigh bone fractures.

Some people have developed unusual fractures in their thigh bone. Symptoms of a fracture may include new or unusual pain in your hip, groin, or thigh.

5. Bone, joint, or muscle pain.

Some people who take bisphosphonates develop severe bone, joint, or muscle pain.

Call your doctor right away if you have any of these side effects.

What is zoledronic acid injection?

Zoledronic acid injection is a prescription medicine used to:

- Treat certain men and women who have Paget’s disease of the bone.

Zoledronic acid injection is not for use in children.

Who should not take zoledronic acid injection?

Do not take zoledronic acid injection if you:

- Have low levels of calcium in your blood
- Have kidney problems
- Are allergic to zoledronic acid or any of its ingredients. A list of ingredients is at the end of this leaflet.

What should I tell my doctor before taking zoledronic acid injection?

Before you start zoledronic acid injection, be sure to talk to your doctor if you:

- Have low blood calcium.
- Have kidney problems.
- Had parathyroid or thyroid surgery (glands in your neck).
- Have been told you have trouble absorbing minerals in your stomach or intestines (malabsorption syndrome) or have had parts of your intestine removed.
- Have asthma (wheezing) from taking aspirin.
- Plan to have dental surgery or teeth removed.
- Are pregnant, or plan to become pregnant. Zoledronic acid injection should not be used if you are pregnant. It is not known if zoledronic acid injection can harm your unborn baby.
- Are breastfeeding or plan to breastfeed. It is not known if zoledronic acid injection passes into your milk and may harm your baby.

Tell your doctor about all the medicines you take, including prescription and non-prescription medicines, vitamins, and herbal supplements. Certain medicines may affect how zoledronic acid injection works.

Especially tell your doctor if you are taking:

- An antibiotic. Certain antibiotic medicines called aminoglycosides may increase the effect of zoledronic acid injection in lowering your blood calcium for a long period of time.
- A diuretic or “water pill”.
- Non-steroidal anti-inflammatory medicines (NSAIDS).

Ask your doctor or pharmacist for a list of these medicines, if you are not sure.

Know the medicines you take. Keep a list of them and show it to your doctor and pharmacist each time you get a new medicine.

How will I receive zoledronic acid injection?

- Your doctor will tell you how often you will receive zoledronic acid injection.
- Zoledronic acid injection is given by infusion into your vein (intravenously). Your infusion should last at least 15 minutes.
- Before you receive zoledronic acid injection, drink at least 2 glasses of fluid (such as water) within a few hours as directed by your doctor.
- You may eat before your treatment with zoledronic acid injection.
- If you miss a dose of zoledronic acid injection, call your doctor or healthcare provider to schedule your next dose.

What are the possible side effects of zoledronic acid injection?

Zoledronic acid injection may cause serious side effects.

- See “What is the most important information I should know about zoledronic acid injection?”

The most common side effects of zoledronic acid injection included:

- Fever
- Pain in your bones, joints or muscles
- Pain in your arms and legs
- Headache
- Flu-like illness (fever, chills, bone, joint, or muscle pain, fatigue)
- Nausea
- Vomiting
- Diarrhea

Talk to your doctor about things you can do to help decrease some of these side effects that might happen with a zoledronic acid infusion.

You may get allergic reactions, such as hives, swelling of your face, lips, tongue, or throat.

Tell your doctor if you have any side effect that bothers you or that does not go away.

These are not all the possible side effects of zoledronic acid injection. For more information, ask your doctor or pharmacist.

Call your doctor for medical advice about side effects. You may report side effects to FDA at 1-800-FDA-1088.

General information about safe and effective use of zoledronic acid injection.

Medicines are sometimes prescribed for purposes other than those listed in a Medication Guide. This Medication Guide summarizes the most important information about zoledronic acid injection. If you would like more information, talk with your doctor. You can ask your doctor or pharmacist for information about zoledronic acid injection that is written for health professionals.

For more information, contact Mylan at 1-877-446-3679 (1-877-4-INFO-RX).

What are the ingredients in zoledronic acid injection?

Active ingredient: zoledronic acid monohydrate.

Inactive ingredients: mannitol and sodium citrate.

This Medication Guide has been approved by the U.S. Food and Drug Administration.

Zometa® is a trademark of Novartis.

Manufactured for:
Mylan Institutional LLC
Morgantown, WV 26505 U.S.A.

Manufactured by:
Mylan Laboratories Limited
Bangalore, India

1034712

OCTOBER 2023

PRINCIPAL DISPLAY PANEL – 5 mg/ 100mL

NDC 67457-619-10

Zoledronic
Acid
Injection

5 mg/100 mL

Solution for
Intravenous Infusion

Do not mix with calcium-containing
solutions.

Administer as a single intravenous
solution through a separate vented
infusion line.

Dispense the accompanying

Medication Guide to each patient.

Rx only Single-Dose Vial

See package insert for DOSAGE and
ADMINISTRATION.

Each vial contains 5.330 mg of zoledronic
acid monohydrate, equivalent to 5 mg
zoledronic acid, USP on an anhydrous
basis, 4950 mg of mannitol USP, 30 mg
of Sodium citrate USP, and water for
injection, USP q.s. to 100 mL.

The pH of the solution is 6 to 7.

After opening, Zoledronic Acid solution is
stable for 24 hours at 2° to 8°C (36° to
46°F).

If refrigerated, allow the refrigerated
solution to reach room temperature
before administration.

Do not mix with calcium-containing
solutions. Administer as a single
intravenous solution through a separate
vented infusion line.

Infusion time must not be less than
15 minutes.

Parenteral drug products should be
inspected visually for particulate matter
and discoloration prior to administration,
whenever solution and container permit.

Store at 20° to 25°C (68° to 77°F);
excursions permitted to 15° to 30°C
(59° to 86°F). [See USP Controlled
Room Temperature.]

Manufactured for:
Mylan Institutional LLC
Morgantown, WV 26505 U.S.A.

Made in India

Code No.:
KR/DRUGS/KTK/28D/18/2016

Mylan.com